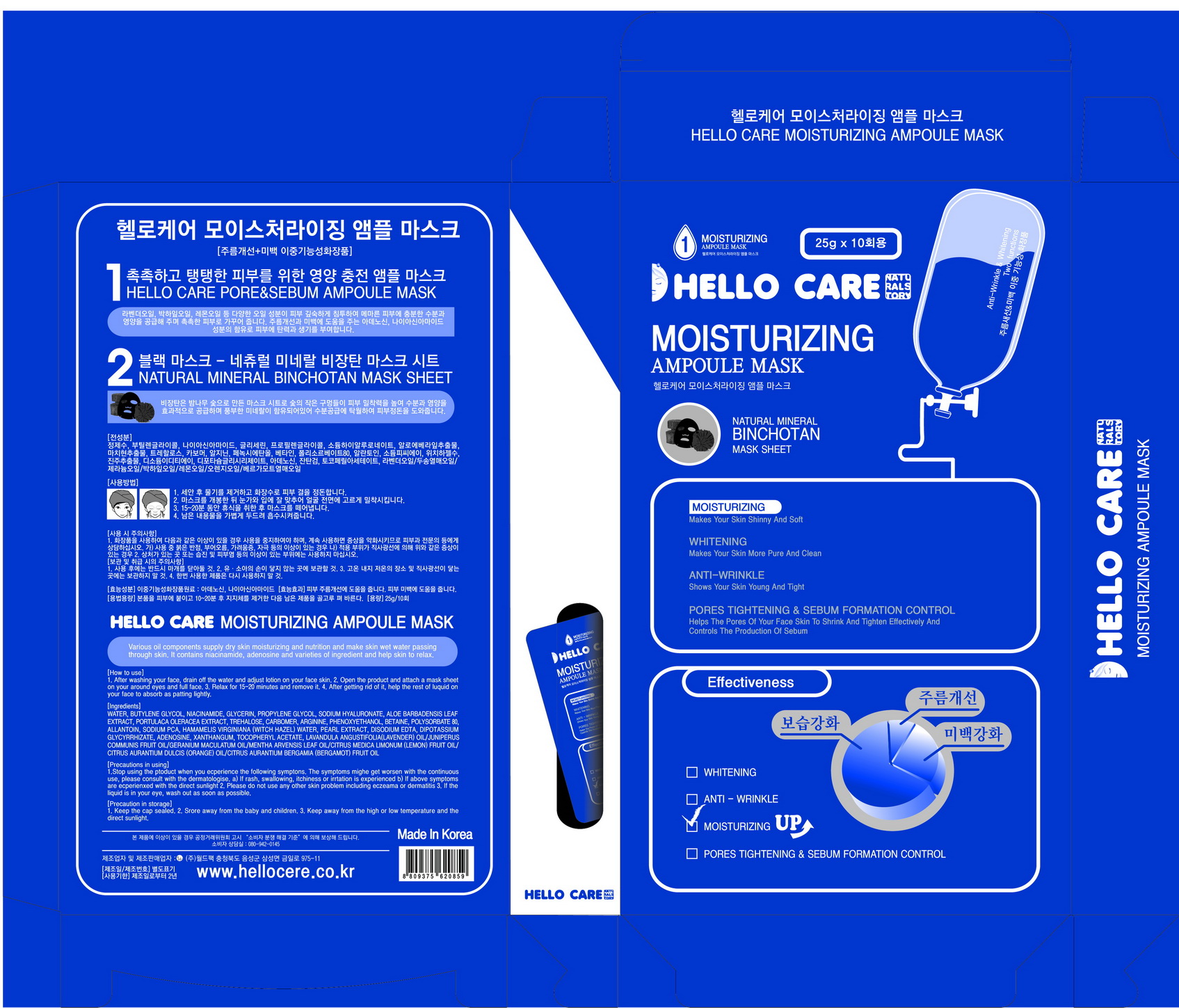 DRUG LABEL: HELLO CARE MOISTURIZING AMPOULE MASK
NDC: 70959-0001 | Form: PATCH
Manufacturer: WORLD PACK CO., LTD.
Category: otc | Type: HUMAN OTC DRUG LABEL
Date: 20160912

ACTIVE INGREDIENTS: NIACINAMIDE 2 g/100 g; ADENOSINE 0.04 g/100 g
INACTIVE INGREDIENTS: BUTYLENE GLYCOL; WATER

Drug Facts

ACTIVE INGREDIENT

Niacinamide, Adenosine

INACTIVE INGREDIENT

Water, Butylene Glycol, Glycerin, etc

PURPOSE

Skin Protectant - Whitening, Anti-Wrinkle, Pores Tightening & Sebum Formation Control

keep out of reach of the children

INDICATIONS AND USAGE

1. After washing your face, drain off the water and adjust lotion on your face skin.
2. Open the product and attach a mask sheet on your around eyes and full face.
3. Relax for 15-20 minutes and remove it.
4. After getting rid of it, help the rest of liquid on your face to absorb as patting lightly.

WARNINGS

1. If the following symptoms occur after product use, stop using the product immediately and consult a dermatologist (continuous use can exacerbate the symptoms).
1) Occurrence of red spots, swelling, itchiness, and other skin irritation
2) If the symptoms above occur after the application area is exposed to direct sunlight
2. Do not use on open wounds, eczema, and other skin irritations
3. Precaution for Storage and Handling
1) Close the lid after use
2) Keep out of reach of infants and children
3) Do not to store in a place with high/low temperature and exposed to direct sunlight

4. Use as avoiding eye areas.

DOSAGE AND ADMINISTRATION

for external use only